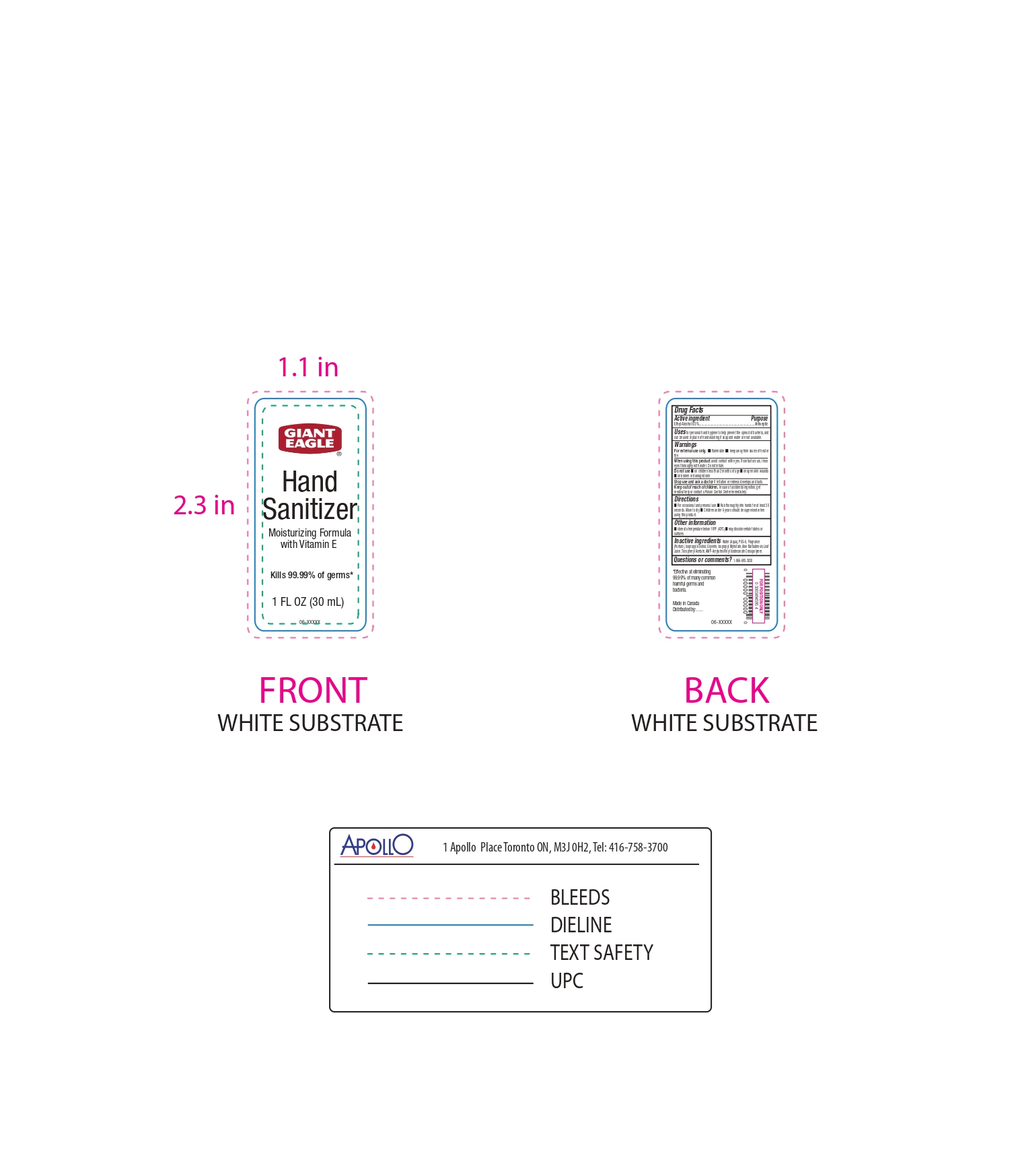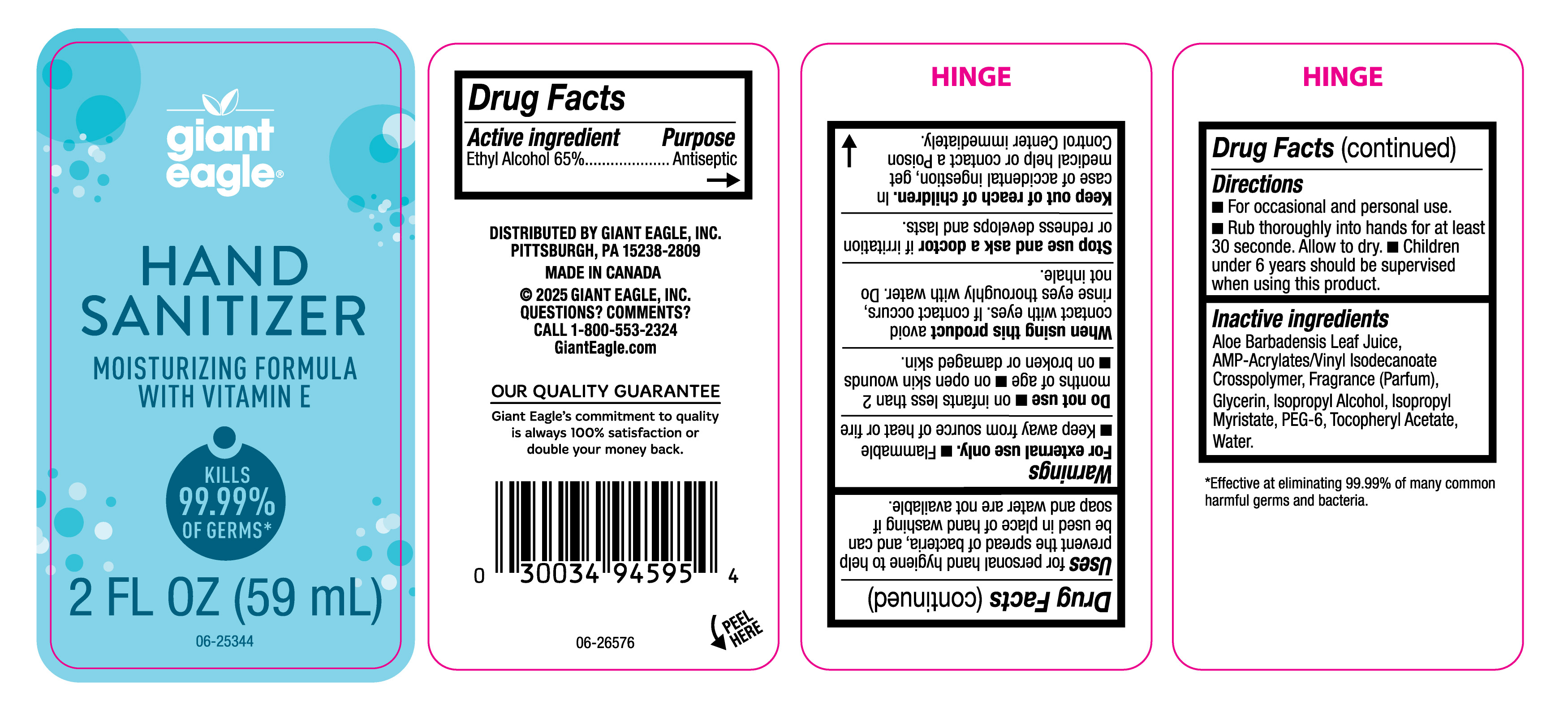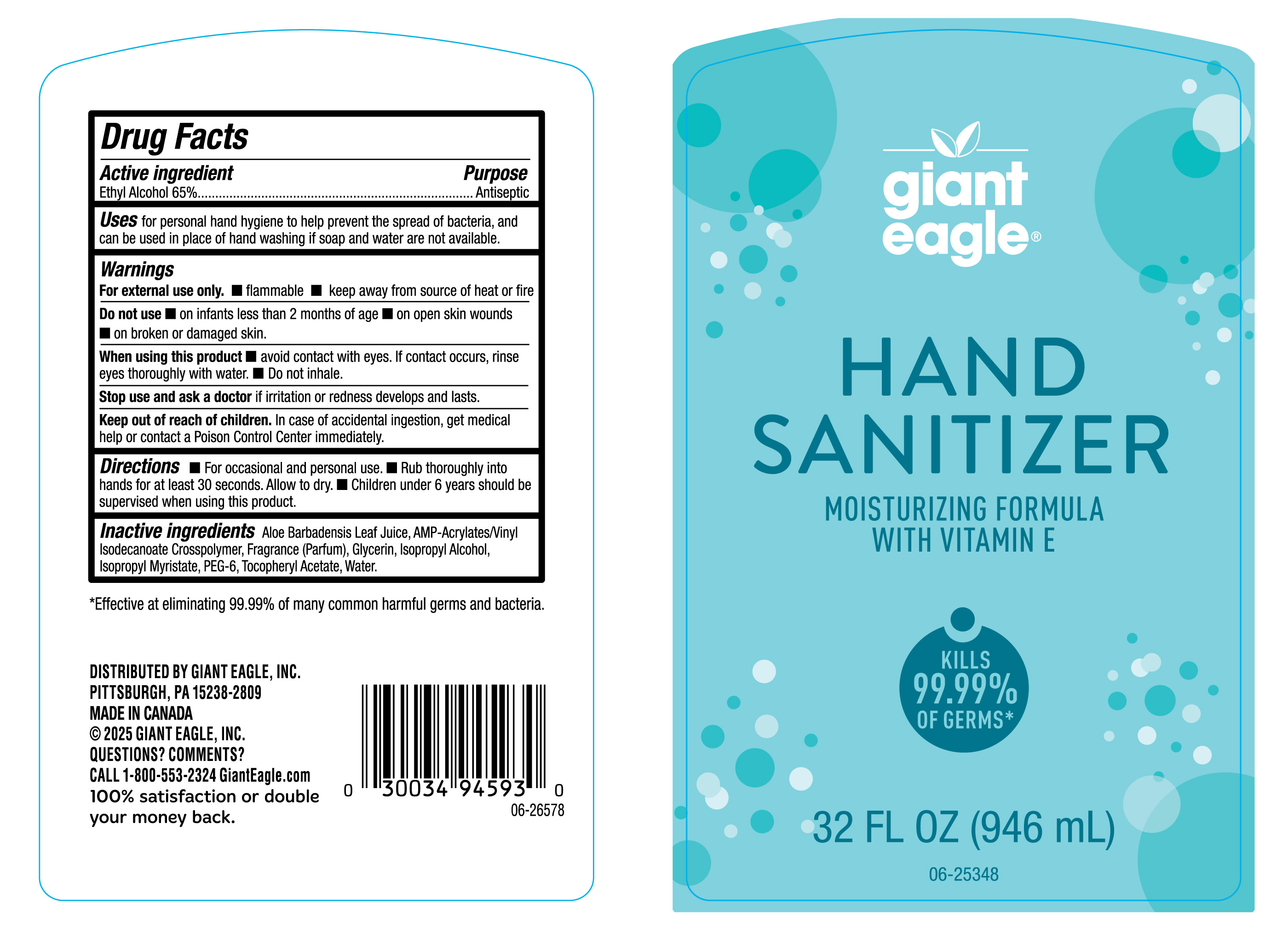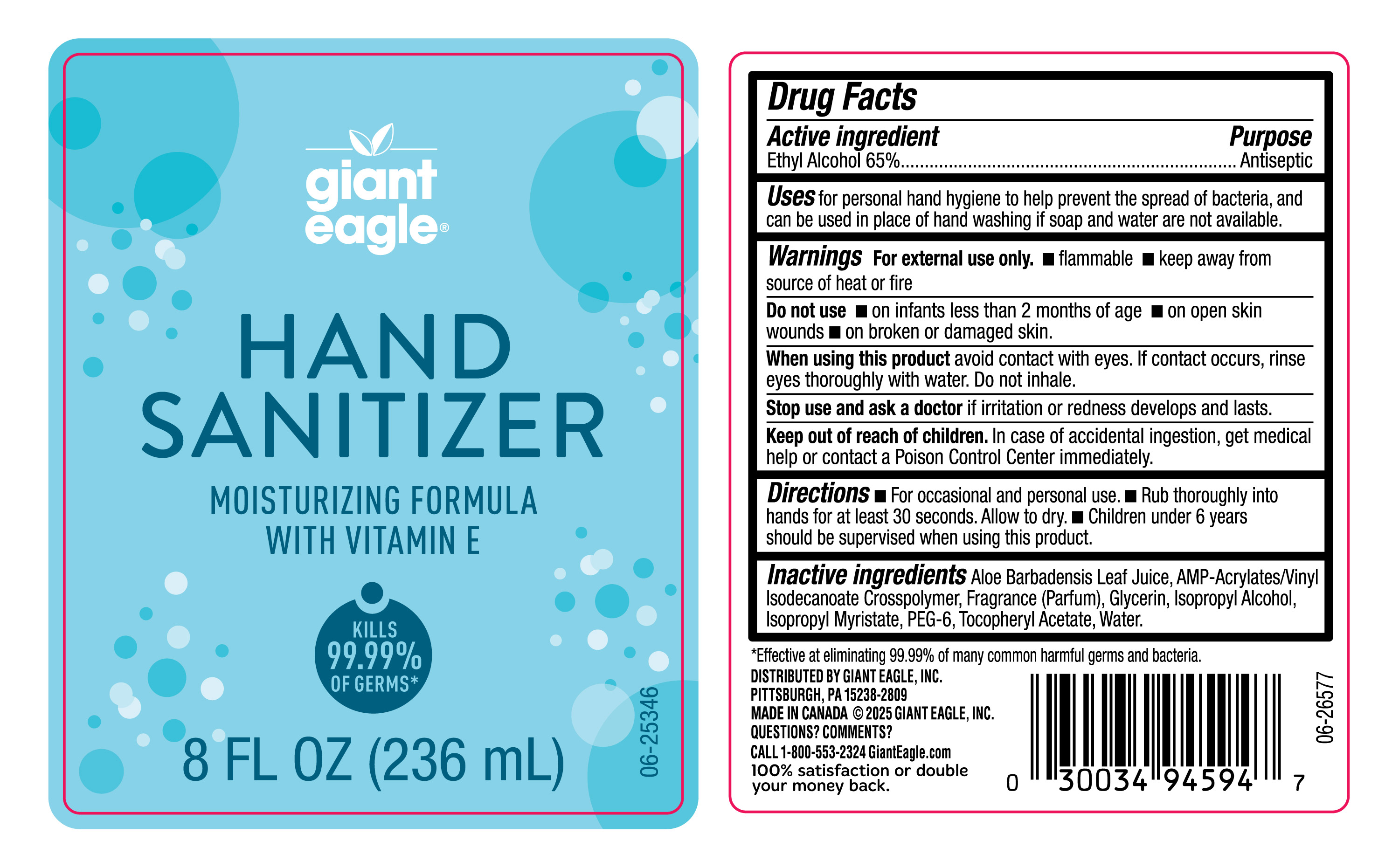 DRUG LABEL: Hand Sanitizer
NDC: 56194-503 | Form: GEL
Manufacturer: Giant Eagle
Category: otc | Type: HUMAN OTC DRUG LABEL
Date: 20250722

ACTIVE INGREDIENTS: ALCOHOL 65 mL/100 mL
INACTIVE INGREDIENTS: FRAGRANCE CLEAN ORC0600327; ISOPROPYL ALCOHOL; ALOE VERA LEAF; .ALPHA.-TOCOPHEROL ACETATE; ACRYLATES/VINYL ISODECANOATE CROSSPOLYMER (10000 MPA.S NEUTRALIZED AT 0.5%); GLYCERIN; PEG-6; WATER; ISOPROPYL MYRISTATE

NDC- 56194-503, Giant Eagle Hand Sanitizer

Active Ingredient

Ethyl Alcohol 65%

Purpose

Antiseptic, Hand Sanitizer

Uses

For personal hand hygiene to help prevent the spread of bacteria, and can be used in place of hand washing if soap and water are not available.

Warnings

For external use only.

- Flammable.
- Keep away from source of heat or fire.

When using this product avoid contact with eyes. If contact occurs, rinse eyes thoroughly with water. Do not inhale.

Do not use

- On children less than 2 months of age
- On open skin wounds
- On broken or damaged skin.

Stop use and ask a doctor If irritation or redness develops and lasts.

Keep out of reach of children. In case of accidental ingestion, get medical help or contact a Poison Control Center immediately.

Directions

- For occasional and personal use.
- Rub thoroughly into hands for at least 30 seconds. Allow to dry.
- Children under 6 years should be supervised when using this product.

Other information

- Store at a temperature below 110ºF (43ºC).
- May discolor certain fabrics or surfaces.

Inactive ingredients

Water (Aqua), PEG-6, Fragrance, (Parfum), Isopropyl Alcohol, Glycerin, Isopropyl Myristate, Aloe Barbadensis Leaf Juice, Tocopheryl Acetate, AMP-Acrylates/Vinyl Isodecanate Crosspolymer.

Questions or comments?

1-866-695-3030